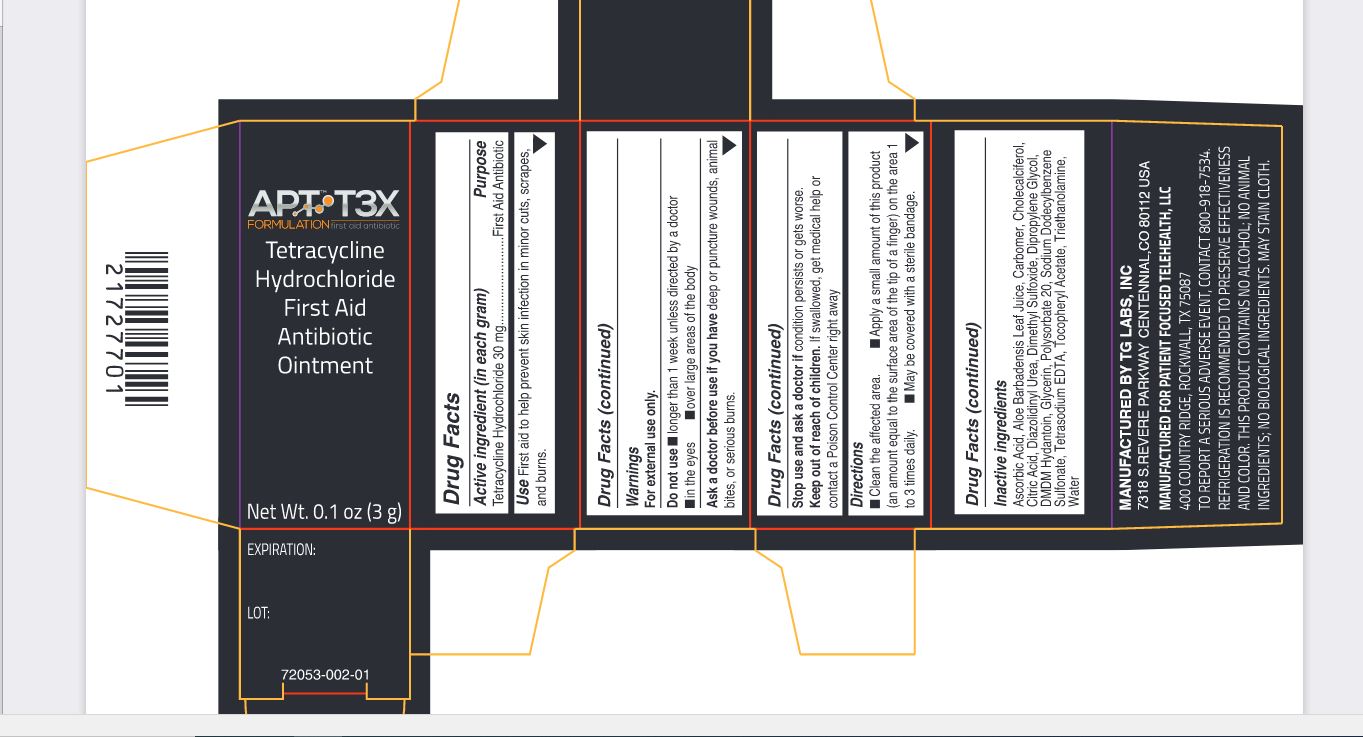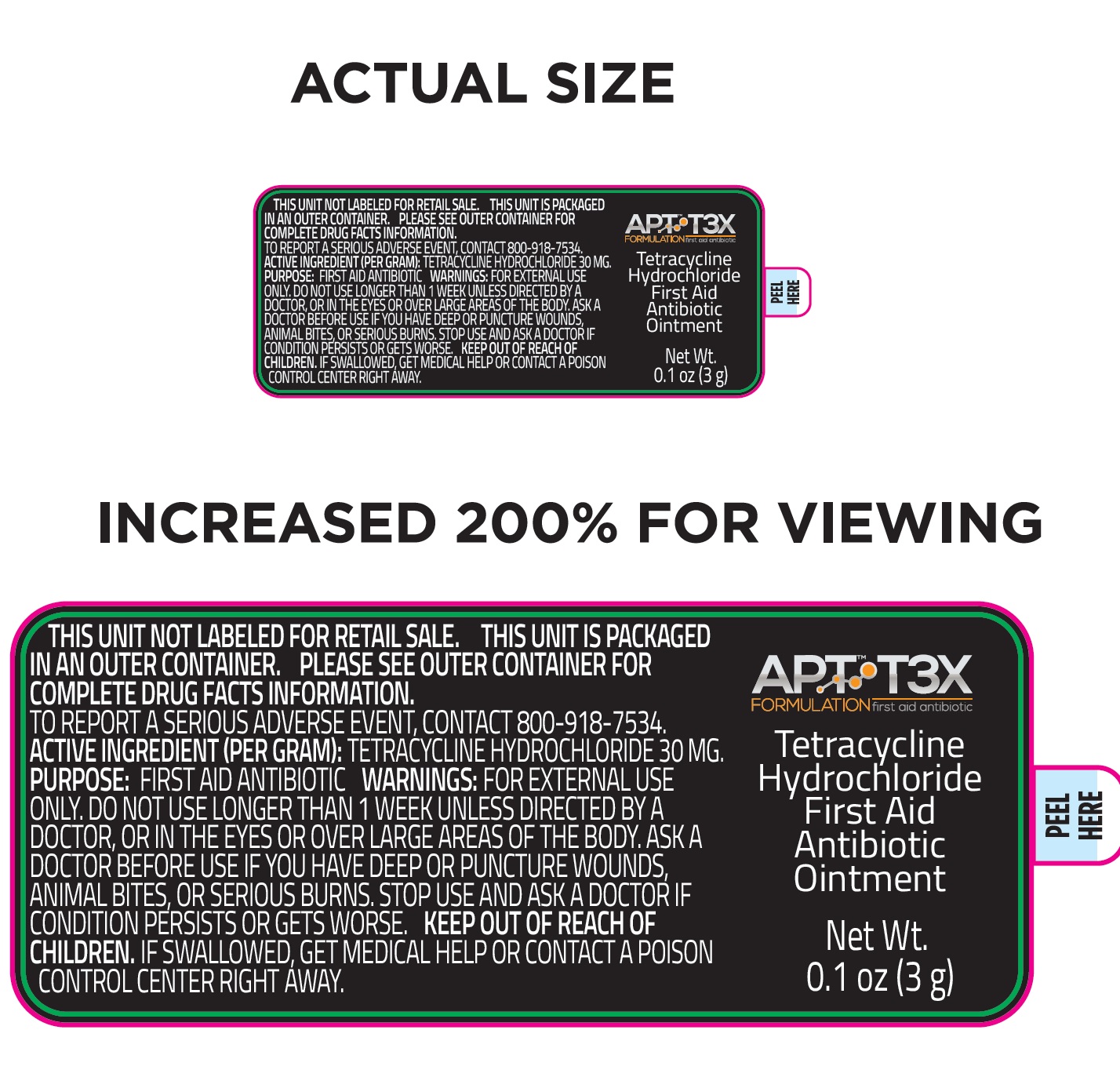 DRUG LABEL: APT T3X Tetracycline Hydrochloride First Aid Antibiotic
NDC: 72053-002 | Form: OINTMENT
Manufacturer: Patient Focused Tele-Health, LLC
Category: otc | Type: HUMAN OTC DRUG LABEL
Date: 20231201

ACTIVE INGREDIENTS: TETRACYCLINE HYDROCHLORIDE 30 mg/1 g
INACTIVE INGREDIENTS: ASCORBIC ACID; ALOE VERA LEAF; CARBOMER HOMOPOLYMER, UNSPECIFIED TYPE; CHOLECALCIFEROL; CITRIC ACID MONOHYDRATE; DIAZOLIDINYL UREA; DIMETHYL SULFOXIDE; DIPROPYLENE GLYCOL; DMDM HYDANTOIN; GLYCERIN; POLYSORBATE 20; SODIUM DODECYLBENZENESULFONATE; EDETATE SODIUM; .ALPHA.-TOCOPHEROL ACETATE; TROLAMINE; WATER

APT T3X Tetracycline Hydrochloride First Aid Antibiotic Ointment

Active ingredient (in each gram)

Tetracycline Hydrochloride 30 mg

Purpose

First Aid Antibiotic

Use

First aid to help prevent skin infection in minor cuts, scrapes, and burns.

Warnings

For external use only.

Do not use

- longer than 1 week unless directed by a doctor
- in the eyes
- over large areas of the body

Ask a doctor before use if you have

deep or puncture wounds, animal bites, or serious burns.

Stop use and ask a doctor if

condition persists or gets worse.

Keep out of reach of children.

If swallowed, get medical help or contact a Poison Control Center right away

Directions

- Clean the affected area.
- Apply a small amount of this product (an amount equal to the surface area of the tip of a finger) on the area 1 to 3 times daily) to 3 times daily.
- May be covered with a sterile bandage.

Inactive ingredients

Ascorbic Acid, Aloe Barbadensis Leaf Juice, Carbomer, Cholecalciferol, Citric Acid, Diazolidinyl Urea, Dimethyl Sulfoxide, Dipropylene Glycol, DMDM Hydantoin, Glycerin, Polysorbate 20, Sodium Dodecylbenzene Sulfonate, Tetrasodium EDTA, Tocopheryl Acetate, Triethanolamine, Water